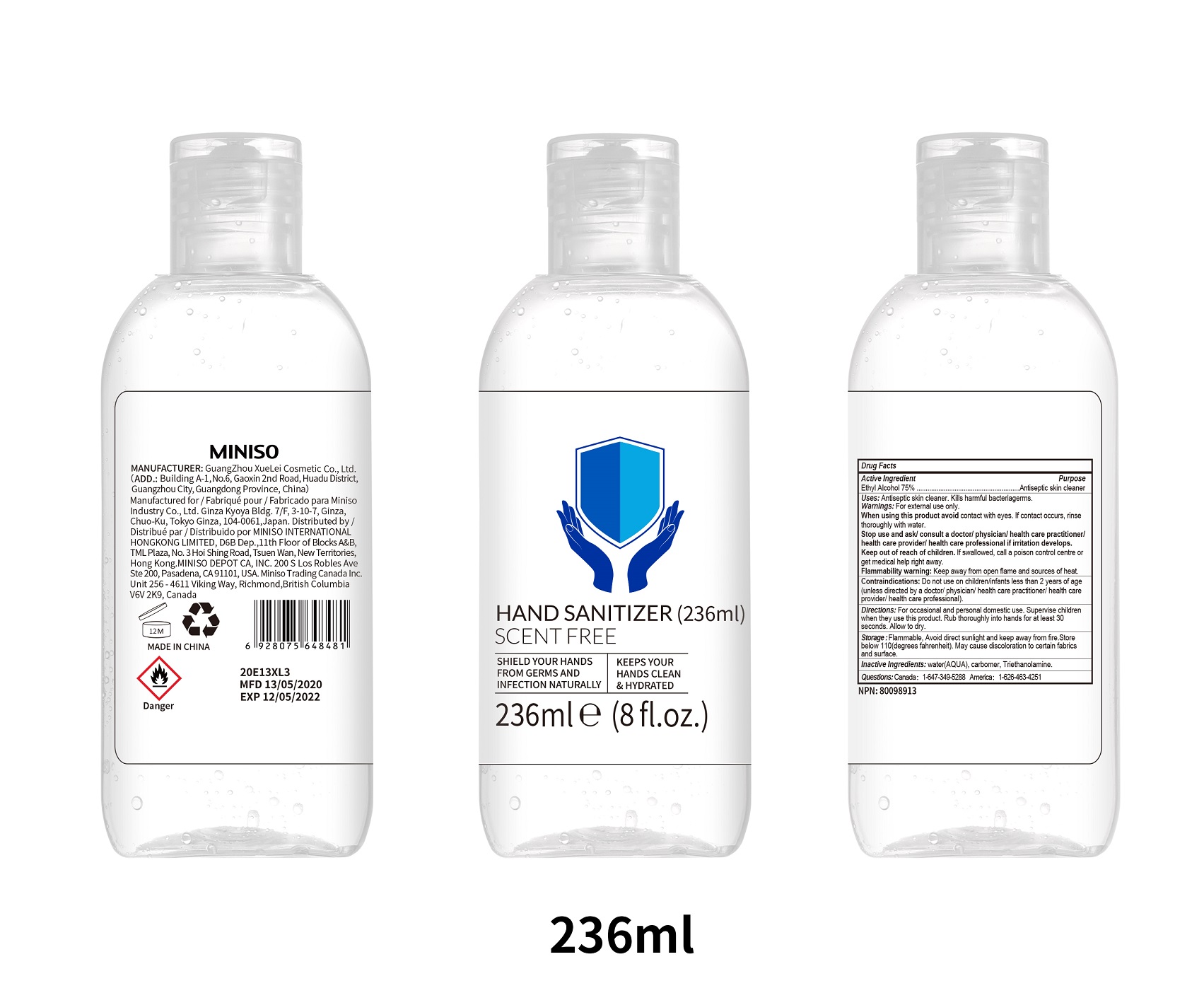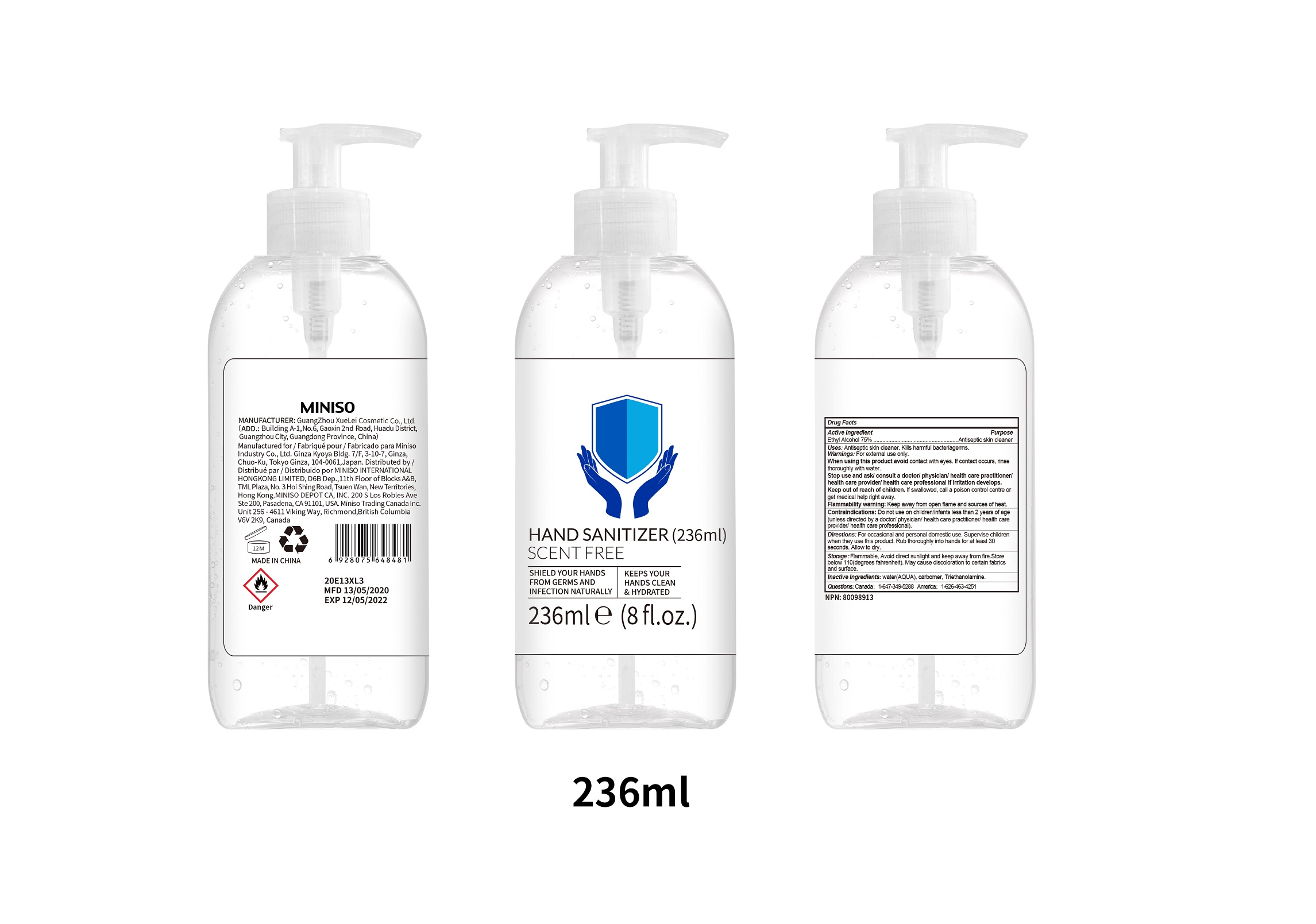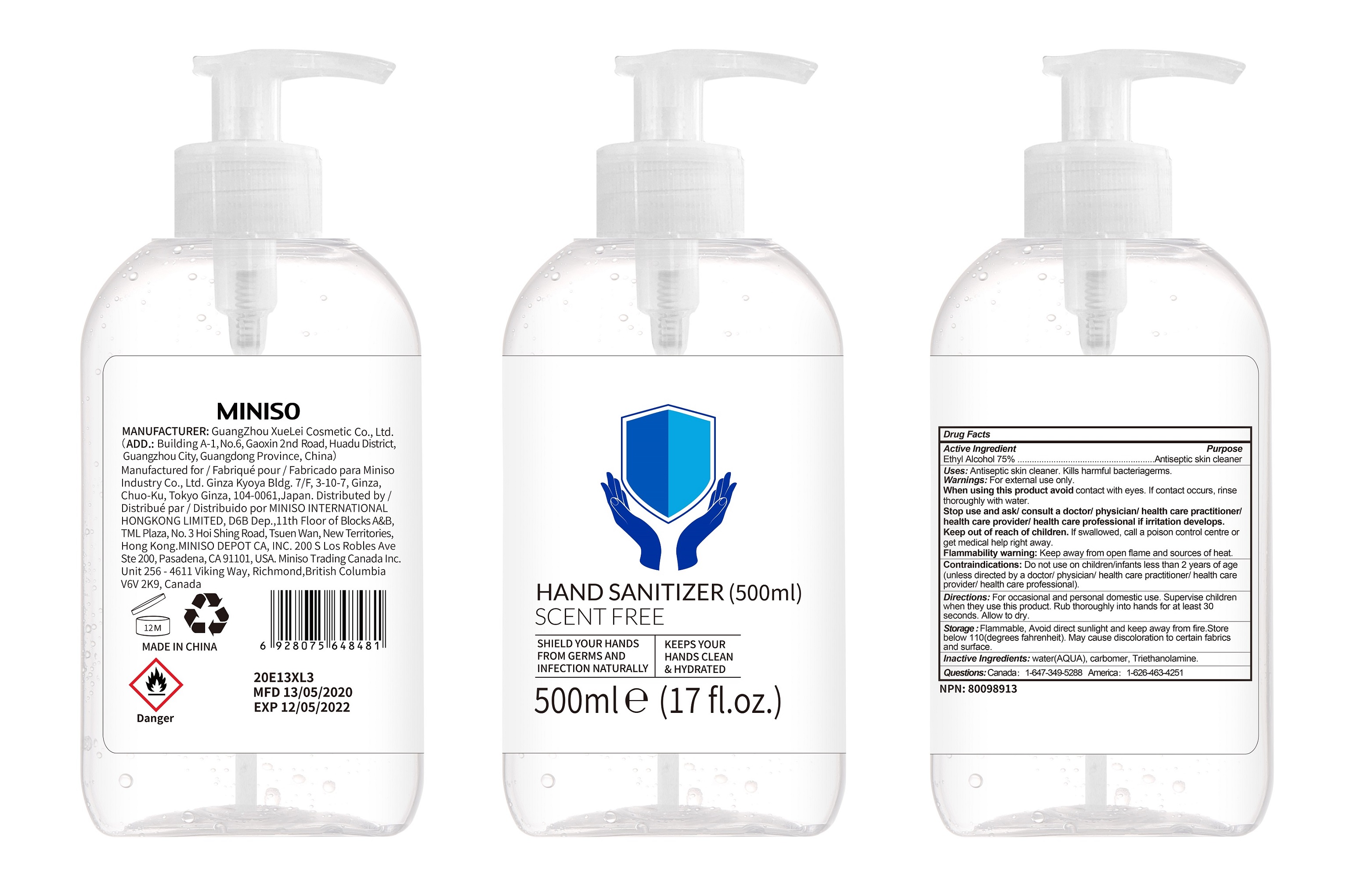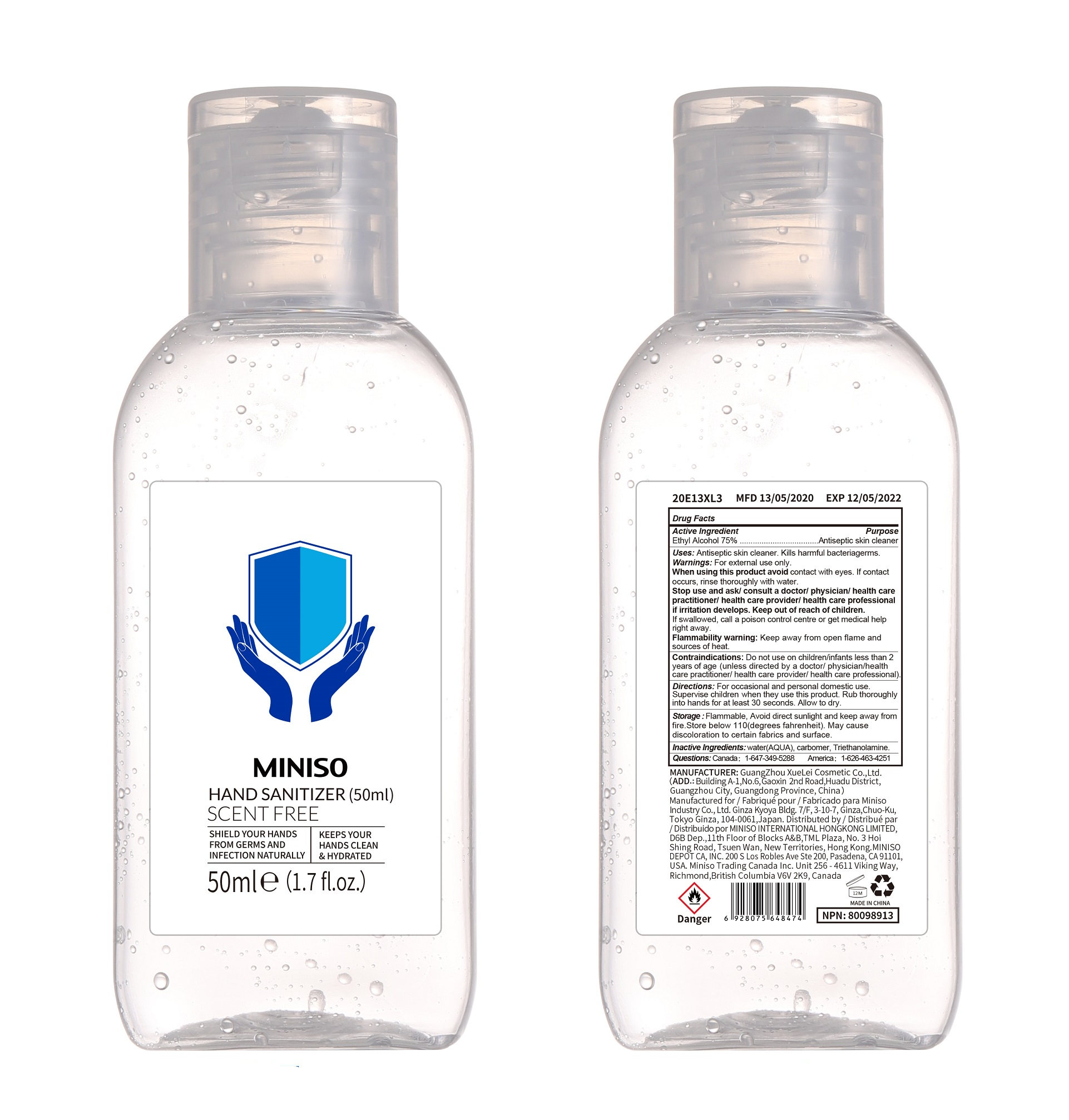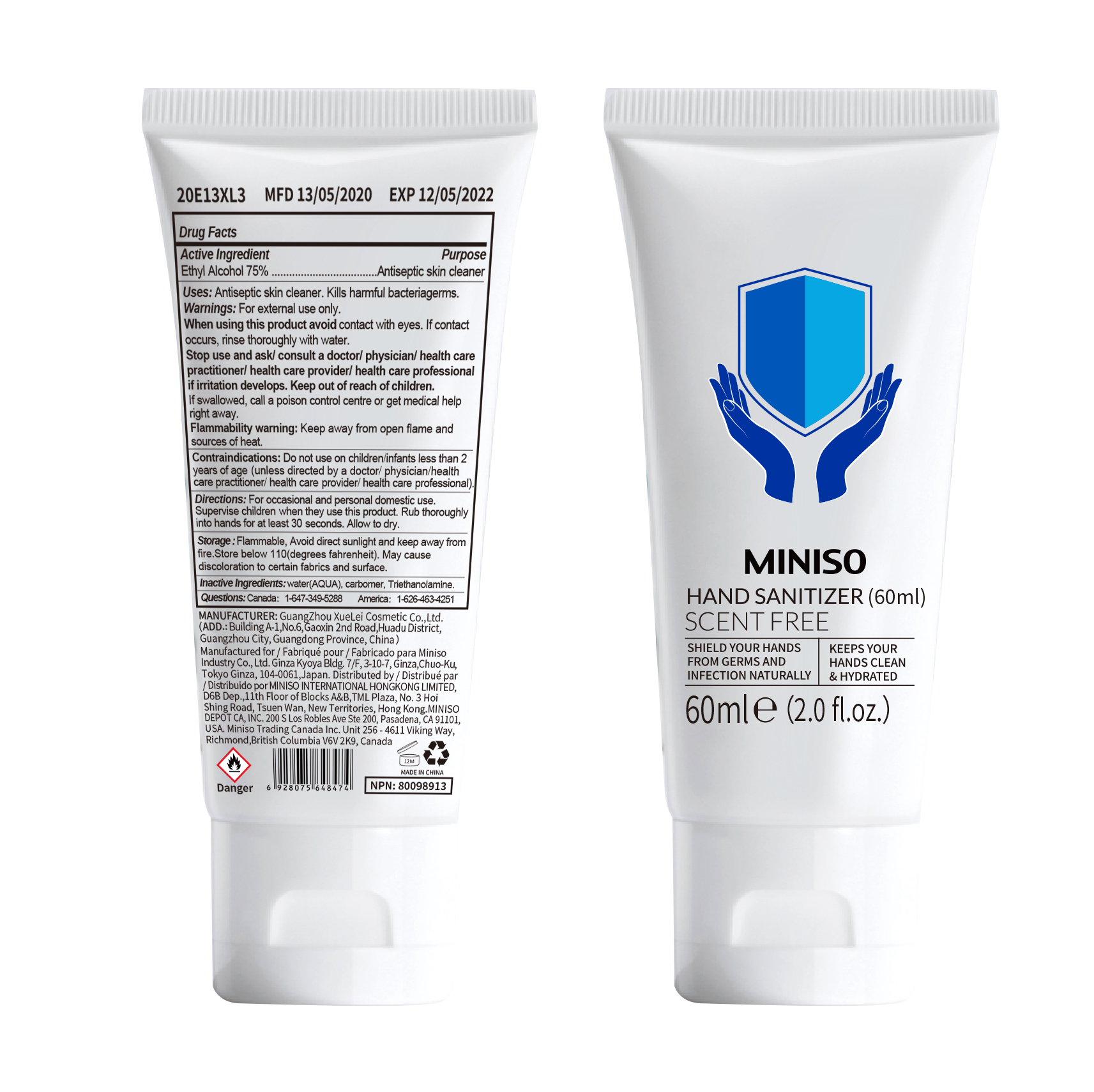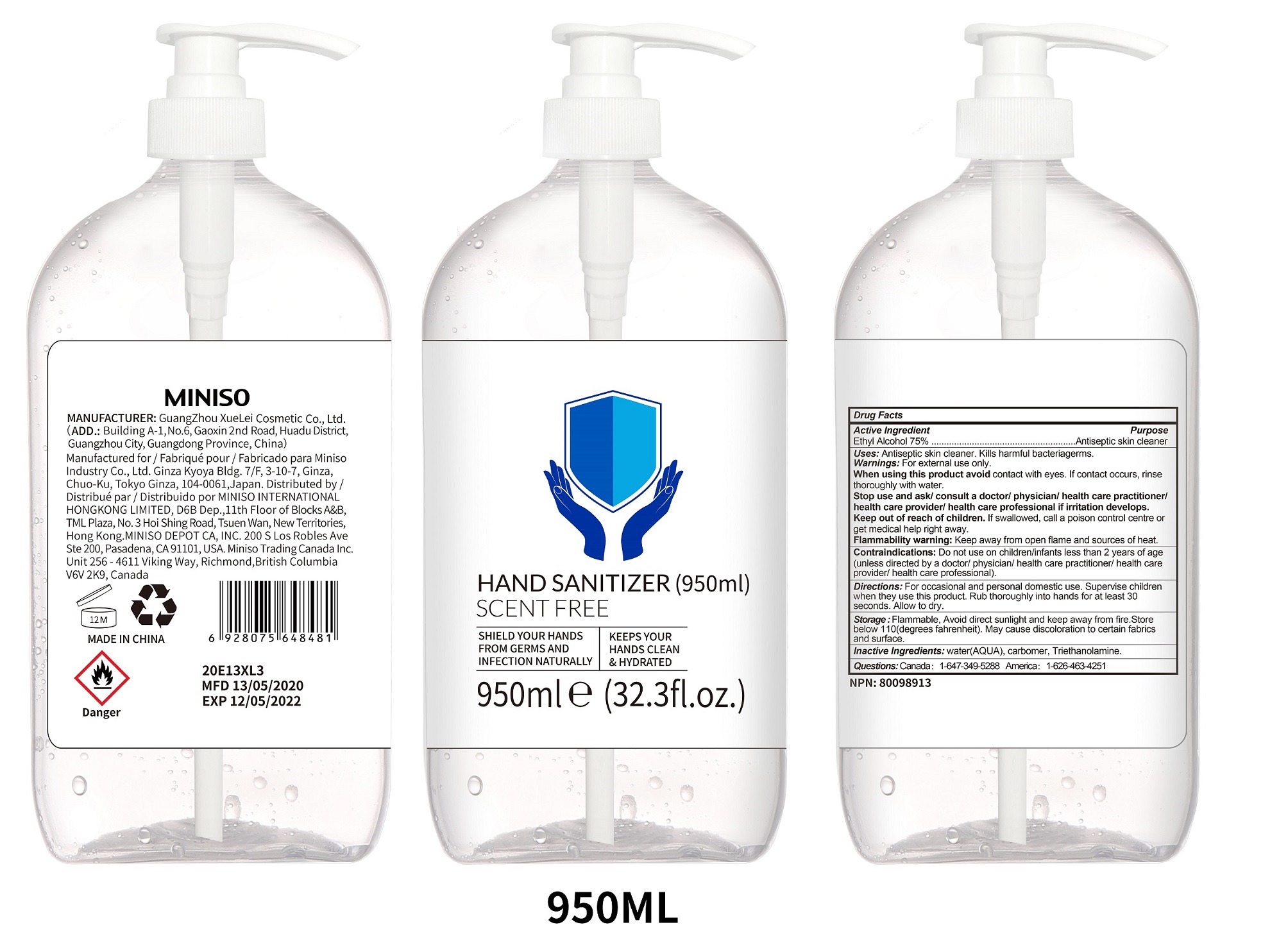 DRUG LABEL: MINISO HAND SANITIZER
NDC: 73950-054 | Form: GEL
Manufacturer: MINISO DEPOT CA, INC. 
Category: otc | Type: HUMAN OTC DRUG LABEL
Date: 20211108

ACTIVE INGREDIENTS: ALCOHOL 75 mL/100 mL
INACTIVE INGREDIENTS: WATER 22.19 g/100 mL; CARBOMER HOMOPOLYMER TYPE B (ALLYL PENTAERYTHRITOL CROSSLINKED) 0.4 g/100 mL; TROLAMINE 0.22 g/100 mL

MINISO HAND SANITIZER

Active Ingredients：

Ethyl Alcohol 75%

Purpose

Antiseptic skin cleaner

Uses:

Antiseptic skin cleaner. Kills harmful bacteria germs.

Warnings:

For external use only.

When using this product avoid contact with eyes. If contact occurs, rinse thoroughly with water. Stop use and ask/consult a doctor/physician/health care practitioner/health care provider/health care professional if irritation develops.

Keep out of reach of children. If swallowed, call a poison centre or get medical help right away.

Flammability warning: Keep away from open flame and sources of heat.

When using this product avoid contact with eyes. If contact occurs, rinse thoroughly with water.

Stop use and ask/consult a doctor/physician/health care practitioner/health care provider/health care professional if irritation develops.

Keep out of reach of children. If swallowed, call a poison centre or get medical help right away.

Contraindications:

Do not use on children/infants less than 2 years of age (unless directed by a doctor/physician/health care practitioner/health care provider/health care professional).

Directions:

For occasional and personal domestic use. Supervise children when they use this product. Rub thoroughly into hands for at least 30 seconds. Allow to dry.

Storage:

Flammable. Avoid direct sunlight and keep away from fire. Store below 110 (degrees fahrenheit). May cause discoloration to certain fabrics and surface.

Inactive Ingredients:

water (AQUA), Carbomer, Triethanolamine.

Package Label

MINISO

HAND SANITIZER (50ml)

SCENT FREE

SHIELD YOUR HANDS FROM GERMS AND INFECTION NATURALLY

KEEPS YOUR HANDS CLEAN & HYDRATED

50ml e (1.7 fl.oz.)

Package Label

MINISO

HAND SANITIZER (60ml)

SCENT FREE

SHIELD YOUR HANDS FROM GERMS AND INFECTION NATURALLY

KEEPS YOUR HANDS CLEAN & HYDRATED

60ml e (2.0 fl.oz.)

NDC: 73950-054-02

Package Label

MINISO

HAND SANITIZER (236ml)

SCENT FREE

SHIELD YOUR HANDS FROM GERMS AND INFECTION NATURALLY

KEEPS YOUR HANDS CLEAN & HYDRATED

236ml e (8 fl.oz.)

Package Label

HAND SANITIZER (500ml)

SCENT FREE

SHIELD YOUR HANDS FROM GERMS AND INFECTION NATURALLY

KEEPS YOUR HANDS CLEAN & HYDRATED

500ml e (17 fl.oz.)

NDC: 73950-054-05

Package Label

MINISO

HAND SANITIZER (950ml)

SCENT FREE

SHIELD YOUR HANDS FROM GERMS AND INFECTION NATURALLY

KEEPS YOUR HANDS CLEAN & HYDRATED

950ml e (32.3 fl.oz.)